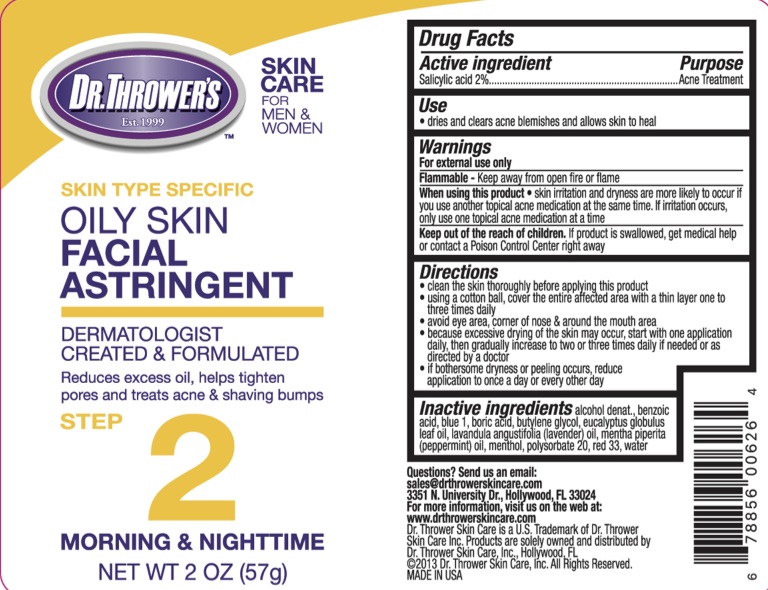 DRUG LABEL: Dr Throwers Oily Skin Facial Astringent
NDC: 72839-611 | Form: LIQUID
Manufacturer: Derma Care Research Labs, LLC
Category: otc | Type: HUMAN OTC DRUG LABEL
Date: 20241220

ACTIVE INGREDIENTS: SALICYLIC ACID 2 g/100 g
INACTIVE INGREDIENTS: BORIC ACID; PEPPERMINT OIL; BUTYLENE GLYCOL; D&C RED NO. 33; FD&C BLUE NO. 1; ALCOHOL; BENZOIC ACID; EUCALYPTUS OIL; LAVENDER OIL; MENTHOL; POLYSORBATE 20; WATER

Dr. Thrower's Oily Skin Facial Astringent

Active Ingredient

Salicylic Acid 2%

Purpose

Acne treatment.

Uses

Dries and clears acne blemishes and allows skin to heal.

Warnings

For external use only.

Flammable--Keep away from open fire or flame.

When using this product skin irritation and dryness are more likely to occur if you use another topical acne medication at the same time. If irritation occurs, only use one topical acne medication at a time.

Keep Out of Reach of Children.

If swallowed, get medical help or contact a Poison Control Center right away.

Directions

- Clean the skin thoroughly before applying this product
- Using a cotton ball, cover the entire affected area with a thin layer one to three times daily
- Avoid eye area, corner of the nose, and around the mouth area
- Because excessive drying of the skin may occur, start with one application daily, then gradually increase to two or three times daily if needed or directed by a doctor
- If bothersome dryness or peeling occurs, reduce application to once a day or every other day

Inactive Ingredients

Alcohol denat., benzoic acid, blue 1, boric acid, butylene glycol, eucalyptus globulus leaf oil, lavandula angustifolia (lavender) oil, mentha piperita (peppermint) oil, menthol, polysorbate 20, red 33, water.